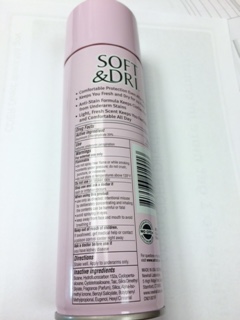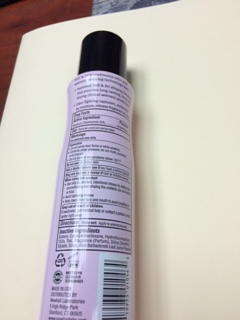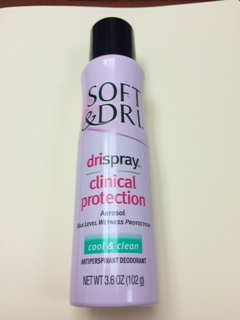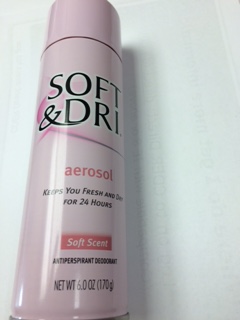 DRUG LABEL: Soft and Dri Soft Scent
NDC: 69752-101 | Form: AEROSOL
Manufacturer: The Village Company
Category: otc | Type: HUMAN OTC DRUG LABEL
Date: 20191217

ACTIVE INGREDIENTS: ALUMINUM CHLOROHYDRATE 200 mg/1 g
INACTIVE INGREDIENTS: BUTANE

SOFT & DRI

- Comfortable protection even after shaving
- Keeps you Fresh and DRY for 24 Hours
- Anti Stain Formual Keeps Clothes Free from Underarm Stains
- Light, Fresh Scent Keeps You Feeling clean and Comfortable All Day

PURPOSE

Antiperspirant Deodorant

Use

reduces underarm perspiration

Warnings For external use only

Flammable

- do not spray near flame or while smoking
- contents under pressure; do not crush, puncture or incinerate
- donot store at a temperature above 120 F

Do not use on broken skin

Stop use and ask a doctor if

rash or irritation occurs

When using this product

- use only as directed; intentional misuse by deliberately concentration and inhaling the contents can be hramful or fatal
- avoid spraying in eyes
- keep away from face and mouth to avoid breating it

Keep out of reach of chlidren

If swallowed, get medical help or contact a posion control center right away

Ask a doctor before use if

you have kidney disease

Directions

Shake Well. Apply to underarms only.

Inactive ingredients

Butane, Hydofluorocarbon 152a, Cyclopentsiloxane, Cyclotetrasiloxane, Talc, Silica Dimethyl Silylate, Fragrance (Parfum), Silica, Alpha-Iso-methyl Ionone, Benzyl Salicylate, Butylphenyl Methylpropional, Eugenol, Hexyl Cinnamal

Active Ingredient

Aluminum Chlorohyrdrate 25%

Purpose

Anitperspirant

Use

Reduces underarm perspiration

Warnings Fore external use only

Flammable

- do not spray near flame or while smoking
- contents under pressure; do not crush, puncture or incinerate
- donot store at a temperature above 120 F

Do not use on broken skin

Keep out of reach of children

If swallowed get medical help, or contact a poison control center right away

Ask a doctor before use if

you have kidney disease

Stop use and ask a doctor if

rash or irritation occurs

When using this product

- use only as directed; intentional misuse by deliberately concentration and inhaling the contents can be hramful or fatal
- avoid spraying in eyes
- keep away from face and mouth to avoid breating it

Directions

Shake well. Apply to underarms only.

Inactive Ingredients

Butane, cylcpentasiloxane, Hydroflurocarbon 152a, Talc, Fragrance (Parfum), Silica Dimethyul Silylate, Silica, Aloe, Bardeandensis Leaf Juice Powder.

DOSAGE AND ADMINISTRATION

Apply to underarms only.

Active Ingredients

Aluminum Chlorohydrate 20%

Soft & Dri aerosol

Keeps you Fresh and Dri

For 24 Hours

Soft Scent

ANTIPERSPIRANT DEODORANT

NET WT 6.0 OZ (170 G)

Soft & Dri Cool& Clean

drispray

clincial Protection

Aerosol

Max Level Wetness Protection

Cool & Clean

ANTIPERSPIRANT DEODORANT

NET WT 3.6 OZ (102G)